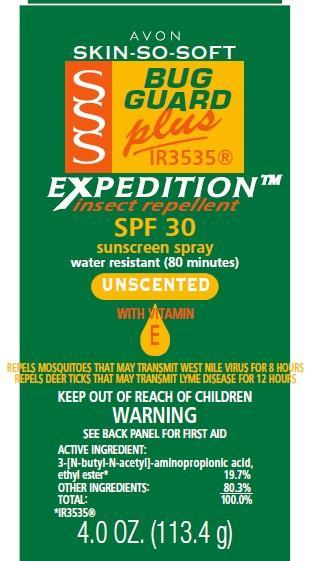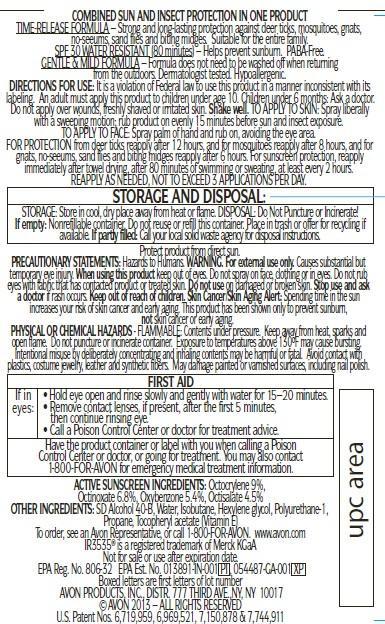 DRUG LABEL: Skin So Soft Bug Guard Plus IR3535
NDC: 10096-0152 | Form: AEROSOL
Manufacturer: Avon Products, Inc
Category: otc | Type: HUMAN OTC DRUG LABEL
Date: 20130212

ACTIVE INGREDIENTS: OCTOCRYLENE 90 mg/1 g; OCTINOXATE 68 mg/1 g; OXYBENZONE 54 mg/1 g; OCTISALATE 45 mg/1 g

INDICATIONS AND USAGE

Helps prevent sunburn.

DOSAGE AND ADMINISTRATION

DIRECTIONS FOR USE: It is a violation of Federal law to use this product in a manner inconsistent with its labeling. An adult must apply this product to children under age 10. Children under 6 months: Ask a doctor. Do not apply over wounds, freshly shaved or irritated skin. Shake well. TO APPLY TO SKIN: Spray liberally with a sweeping motion; rub product on evenly 15 minutes before sun and insect exposure. TO APPLY TO FACE: Spray palm of hand and rub on, avoiding the eye area. FOR PROTECTION from deer ticks reapply after 12 hours, and for mosquitoes reapply after 8 hours, and for gnats, no-seeums, sand flies and biting midges reapply after 6 hours. For sunscreen protection, reapply immediately after towel drying, after 80 minutes of swimming or sweating, at least every 2 hours. REAPPLY AS NEEDED, NOT TO EXCEED 3 APPLICATIONS PER DAY.

STORAGE AND HANDLING

STORAGE: Store in cool, dry place away from heat or flame.

Protect product from direct sun.

WARNINGS

WARNING. For external use only. Causes substantial but temporary eye injury. When using this product keep out of eyes. Do not spray on face, clothing or in eyes. Do not rub eyes with fabric that has contacted product or treated skin. Do not use on damaged or broken skin. Stop use and ask a doctor if rash occurs. Keep out of reach of children. Skin Cancer/Skin Aging Alert: Spending time in the sun increases your risk of skin cancer and early aging. This product has been shown only to prevent sunburn, not skin cancer or early aging.

ACTIVE INGREDIENT

ACTIVE SUNSCREEN INGREDIENTS: Octocrylene 9%, Octinoxate 6.8%, Oxybenzone 5.4%, Octisalate 4.5%

INACTIVE INGREDIENT

OTHER INGREDIENTS: SD Alcohol 40-B, Water, Isobutane, Hexylene glycol, Polyurethane-1, Propane, Tocopheryl acetate (Vitamin E)